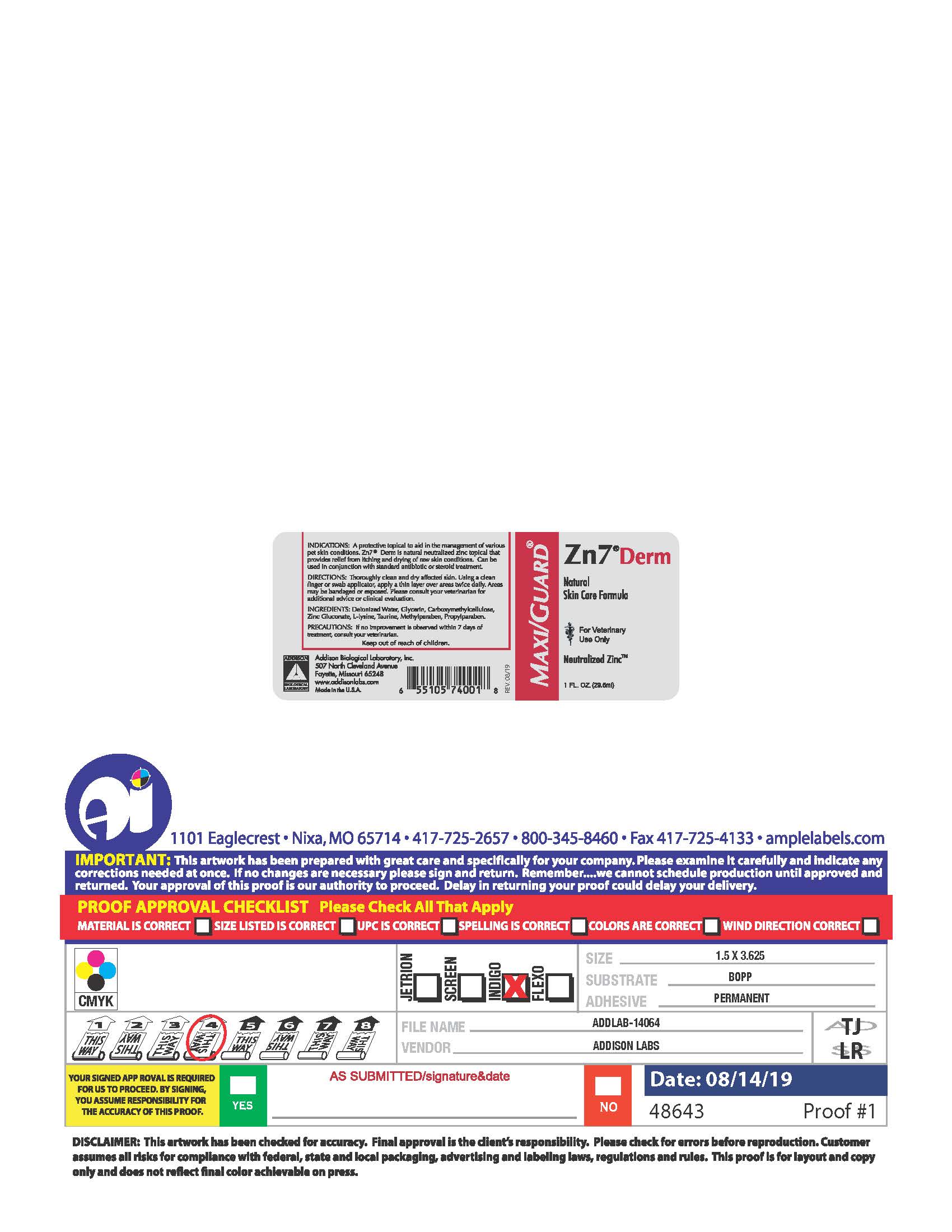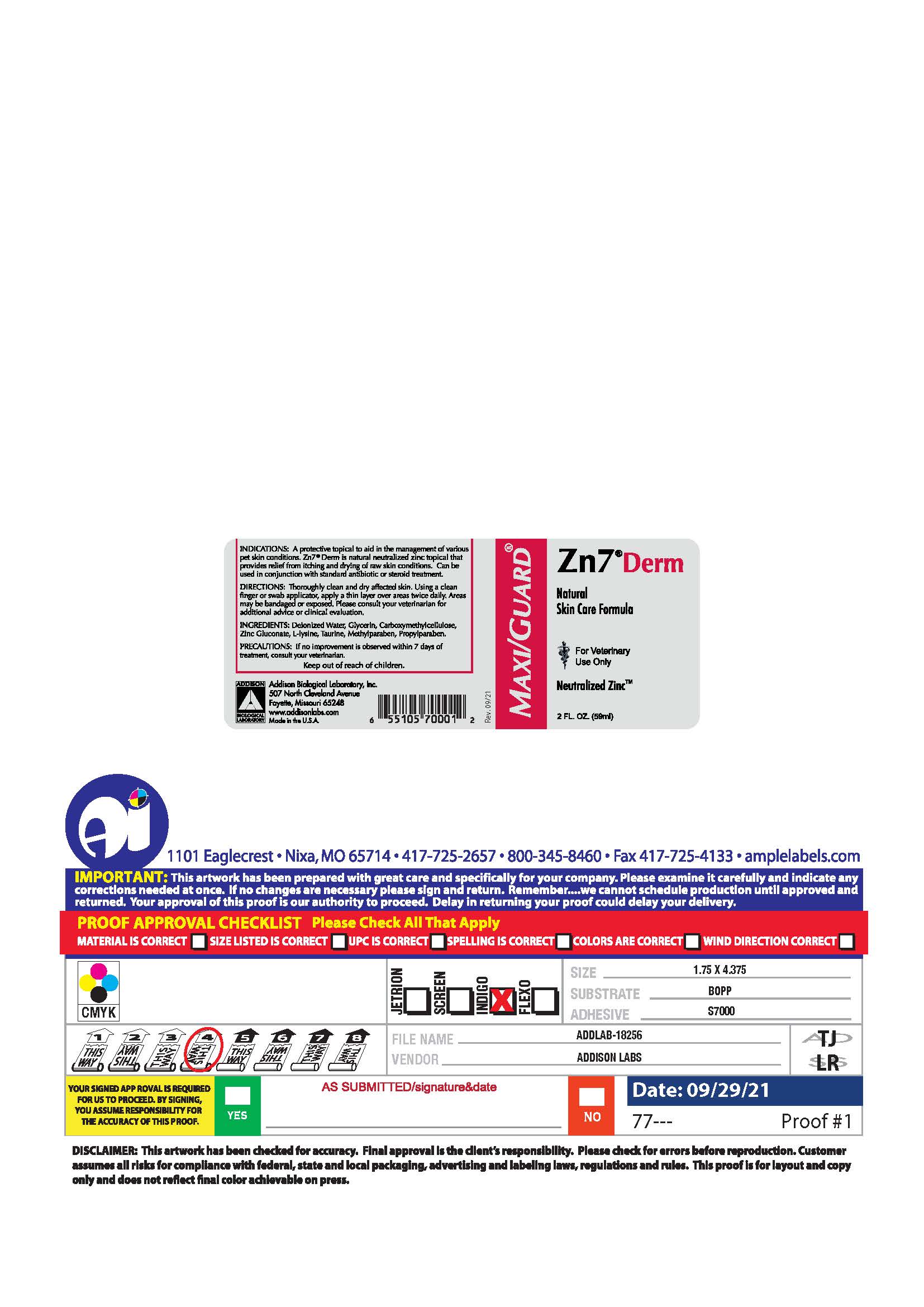 DRUG LABEL: Zn7 Derm
NDC: 86045-6000 | Form: GEL
Manufacturer: Addison Biological Laboratory, Inc.
Category: animal | Type: OTC ANIMAL DRUG LABEL
Date: 20251201

ACTIVE INGREDIENTS: ZINC GLUCONATE .011 g/1 mL
INACTIVE INGREDIENTS: WATER; TAURINE; METHYLPARABEN; PROPYLPARABEN; LYSINE; GLYCERIN; CARBOXYMETHYLCELLULOSE

Zn7®Derm

INDICATIONS AND USAGE

INDICATIONS: A protective topical to aid in the management of various pet skin conditions. Zn7Derm is natural neutralized zinc topical that provides relief from itching and drying of raw skin conditions. Can be used in conjunction with standard antibiotic or steroid treatment.

INSTRUCTIONS FOR USE

DIRECTIONS: Thoroughly clean and dry affected skin. Using a clean finger or swab applicator, apply a thin layer over the areas twice daily. Areas may be bandaged or exposed. Please consult your veterinarian for additional advice or clinical evaluation.

INGREDIENTS: Deionized Water, Glycerin, Carboxymethycellulose, Zinc Gluconate, L-Lysine, Taurine, Methylparaben, Propylparaben.

PRECAUTIONS

PRECAUTIONS:If no improvement is observed within 7 days of treatment, consult your veterinarian.

Keep out of reach of children.

Addison Biological Laboratory, Inc.
507 North Cleveland Avenue
Fayette, Missouri 65248
www.addisonlabs.com
MADE IN THE U.S.A.
Rev. 07/17

PACKAGE LABEL

MAXI/GUARD®

Zn7®Derm
Natural
Skin Care Formula
For Veterinary
Use Only
Neutralized Zinc™
1 FL. OZ. (29.5 ml)
INDICATIONS: A protective topical to aid in the management of various pet skin conditions. Zn7®Derm is natural neutralized zinc topical that provides relief from itching and drying of raw skin conditions. Can be used in conjunction with standard antibiotic or steroid treatment.
DIRECTIONS: Thoroughly clean and dry affected skin. Using a clean finger or swab applicator, apply a thin layer over the areas twice daily. Areas may be bandaged or exposed. Please consult your veterinarian for additional advice or clinical evaluation.
INGREDIENTS: Deionized Water, Glycerin, Carboxymethycellulose, Zinc Gluconate, L-Lysine, Taurine, Methylparaben, Propylparaben.
PRECAUTIONS: If no improvement is observed within 7 days of treatment, consult your veterinarian.
Keep out of reach of children.
Addison Biological Laboratory, Inc.
507 North Cleveland Avenue
Fayette, Missouri 65248
www.addisonlabs.com
MADE IN THE U.S.A.
Rev. 08/19

PACKAGE LABEL

MAXI/GUARD®

Zn7®Derm
Natural
Skin Care Formula
For Veternary
Use Only
Neutralized Zinc™
2 FL. OZ. (59 ml)
INDICATIONS: A protective topical to aid in the management of various pet skin conditions. Zn7®Derm is natural neutralized zinc topical that provides relief from itching and drying of raw skin conditions. Can be used in conjunction with standard antibiotic or steroid treatment.
DIRECTIONS: Thoroughly clean and dry affected skin. Using a clean finger or swab applicator, apply a thin layer over the areas twice daily. Areas may be bandaged or exposed. Please consult your veterinarian for additional advice or clinical evaluation.
INGREDIENTS: Deionized Water, Glycerin, Carboxymethycellulose, Zinc Gluconate, L-Lysine, Taurine, Methylparaben, Propylparaben.
PRECAUTIONS: If no improvement is observed within 7 days of treatment, consult your veterinarian.
Keep out of reach of children.
Addison Biological Laboratory, Inc.
507 North Cleveland Avenue
Fayette, Missouri 65248
www.addisonlabs.com
MADE IN THE U.S.A.
Rev. 09/21